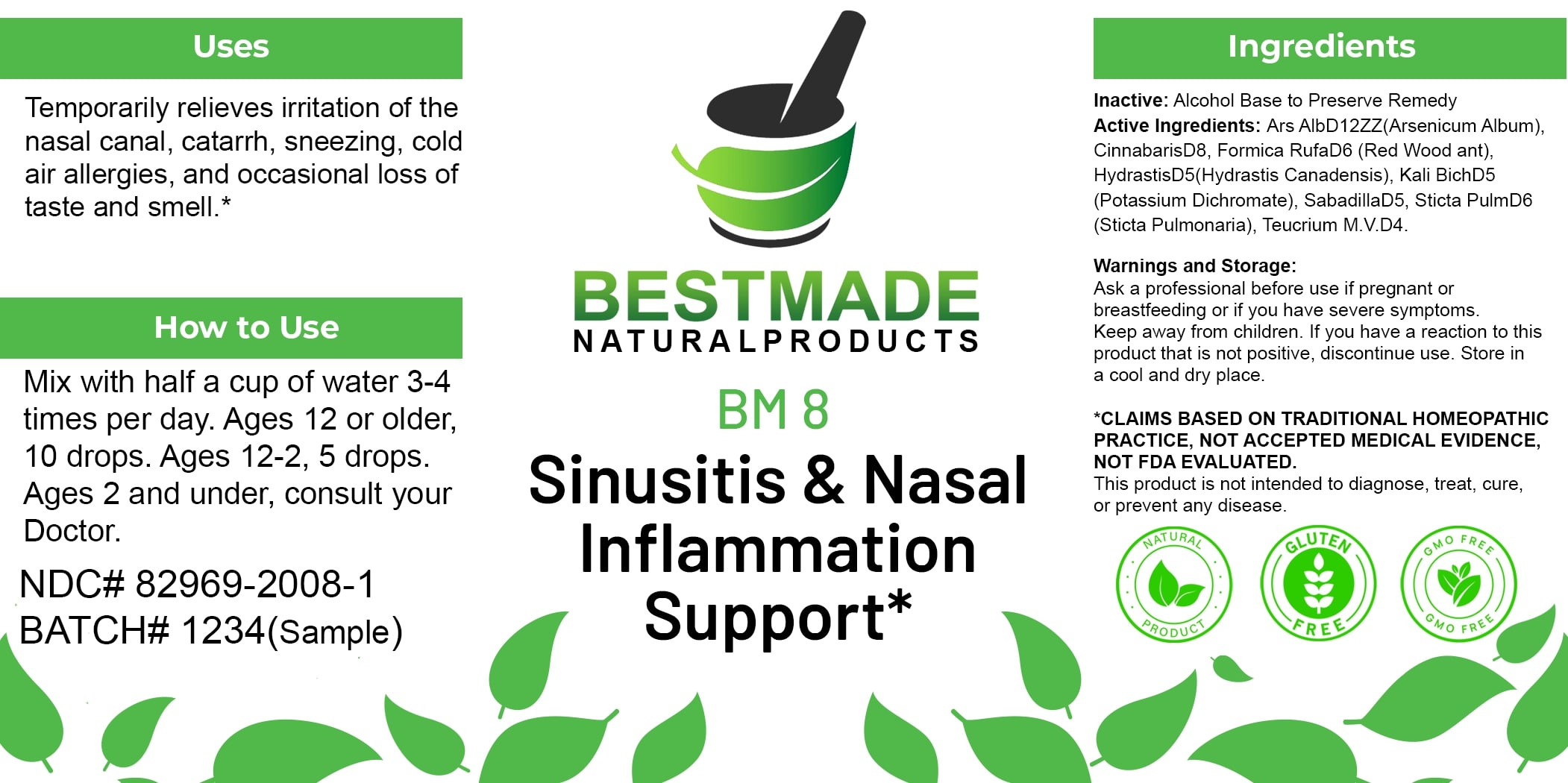 DRUG LABEL: Bestmade Natural Products BM8
NDC: 82969-2008 | Form: LIQUID
Manufacturer: Bestmade Natural Products
Category: homeopathic | Type: HUMAN OTC DRUG LABEL
Date: 20250122

ACTIVE INGREDIENTS: LOBARIA PULMONARIA 30 [hp_C]/30 [hp_C]; ARSENIC TRIOXIDE 30 [hp_C]/30 [hp_C]; GOLDENSEAL 30 [hp_C]/30 [hp_C]; POTASSIUM DICHROMATE 30 [hp_C]/30 [hp_C]; SCHOENOCAULON OFFICINALE SEED 30 [hp_C]/30 [hp_C]; TEUCRIUM MARUM 30 [hp_C]/30 [hp_C]; FORMICA RUFA 30 [hp_C]/30 [hp_C]; MERCURIC SULFIDE 30 [hp_C]/30 [hp_C]
INACTIVE INGREDIENTS: ALCOHOL 30 [hp_C]/30 [hp_C]

BM8

Inactive:

Alcohol Base to Preserve Remedy

INDICATIONS AND USAGE

Temporarily relieves irritation of the nasal canal, catarrh, sneezing, cold air allergies, and occasional loss of taste and smell.*

*CLAIMS BASED ON TRADITIONAL HOMEOPATHIC PRACTICE, NOT ACCEPTED MEDICAL EVIDENCE, NOT FDA EVALUATED.
This product is not intended to diagnose, treat, cure, or prevent any disease.

Active Ingredients:

Ars AlbD12ZZ (Arsenicum Album)
CinnabarisD8
Formica RufaD6 (Red Wood ant)
HydrastisD5 (Hydrastis Canadensis)
Kali BichD5 (Potassium Dichromate)
SabadillaD5
Sticta PulmD6 (Sticta Pulmonaria)
Teucrium M.V.D4

KEEP OUT OF REACH OF CHILDREN

Warnings and Storage

Ask a professional before use if pregnant or breastfeeding or if you have severe symptoms.

Keep away from children. If you have a reaction to this product that is not positive, discontinue use. Store in a cool and dry place.

PURPOSE

Temporarily relieves irritation of the nasal canal, catarrh, sneezing, cold air allergies, and occasional loss of taste and smell.*

*CLAIMS BASED ON TRADITIONAL HOMEOPATHIC PRACTICE, NOT ACCEPTED MEDICAL EVIDENCE, NOT FDA EVALUATED.
This product is not intended to diagnose, treat, cure, or prevent any disease.

Warnings and Storage

Ask a professional before use if pregnant or breastfeeding or if you have severe symptoms. Keep away from children. If you have a reaction to this product that is not positive, discontinue use. Store in a cool and dry place.

*CLAIMS BASED ON TRADITIONAL HOMEOPATHIC PRACTICE, NOT ACCEPTED MEDICAL EVIDENCE, NOT FDA EVALUATED.
This product is not intended to diagnose, treat, cure, or prevent any disease.

DOSAGE AND ADMINISTRATION

How to Use

Mix with half a cup of water 3-4 times per day. Ages 12 or older: 10 drops. Ages 12-2: 5 drops. Ages 2 and under: consult your Doctor.

Entire package label